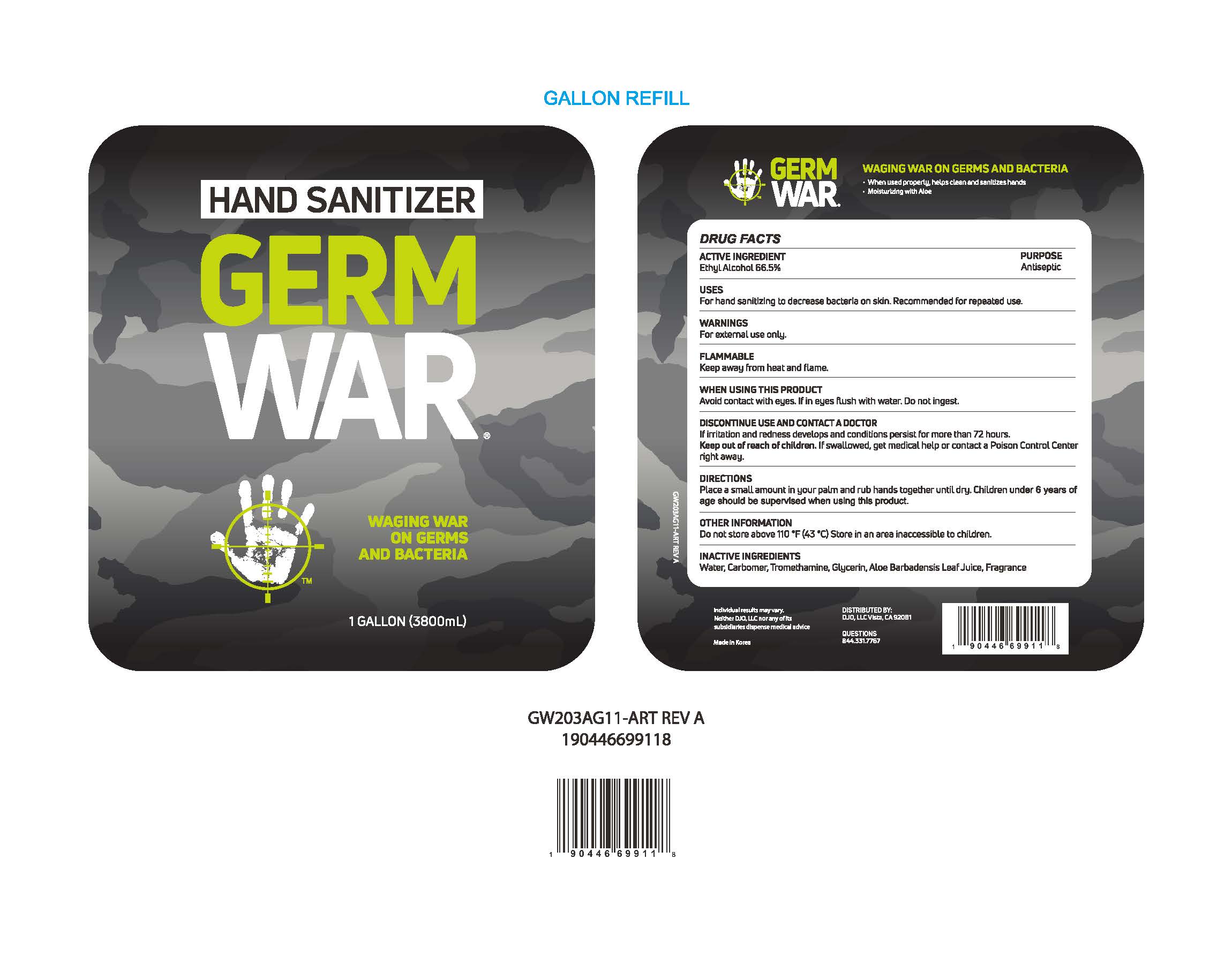 DRUG LABEL: GERM WAR HAND SANITIZER gel
NDC: 73793-0010 | Form: GEL
Manufacturer: SKINFARM	
Category: otc | Type: HUMAN OTC DRUG LABEL
Date: 20200908

ACTIVE INGREDIENTS: ALCOHOL 66.5 g/100 mL
INACTIVE INGREDIENTS: TROLAMINE; CARBOMER HOMOPOLYMER, UNSPECIFIED TYPE; GLYCERIN; WATER; ALOE VERA LEAF

Drug Facts

ACTIVE INGREDIENT

Alcohol

INACTIVE INGREDIENT

Water, Carbomer, Trometharmine, Glycerin, Aloe Barbadensis Leaf Juice, Fragrance

PURPOSE

Antiseptic

KEEP OUT OF REACH OF THE CHILDREN

INDICATIONS AND USAGE

For the external use only

WARNINGS

For external use only.
Avoid contact with eyes. If introduced to eyes, flush with water.
Do not ingest.
Discontinue use and contact a doctor if irritation and redness develops and
condition persist for more than 72 hours.
Keep out of reach of children. if swallowed, get medial help or contact a Poison
Control Center right away

DOSAGE AND ADMINISTRATION

Place a small amount in your palm and rub hands together until dry. Children under
6 years of age should be supervised when using this product.